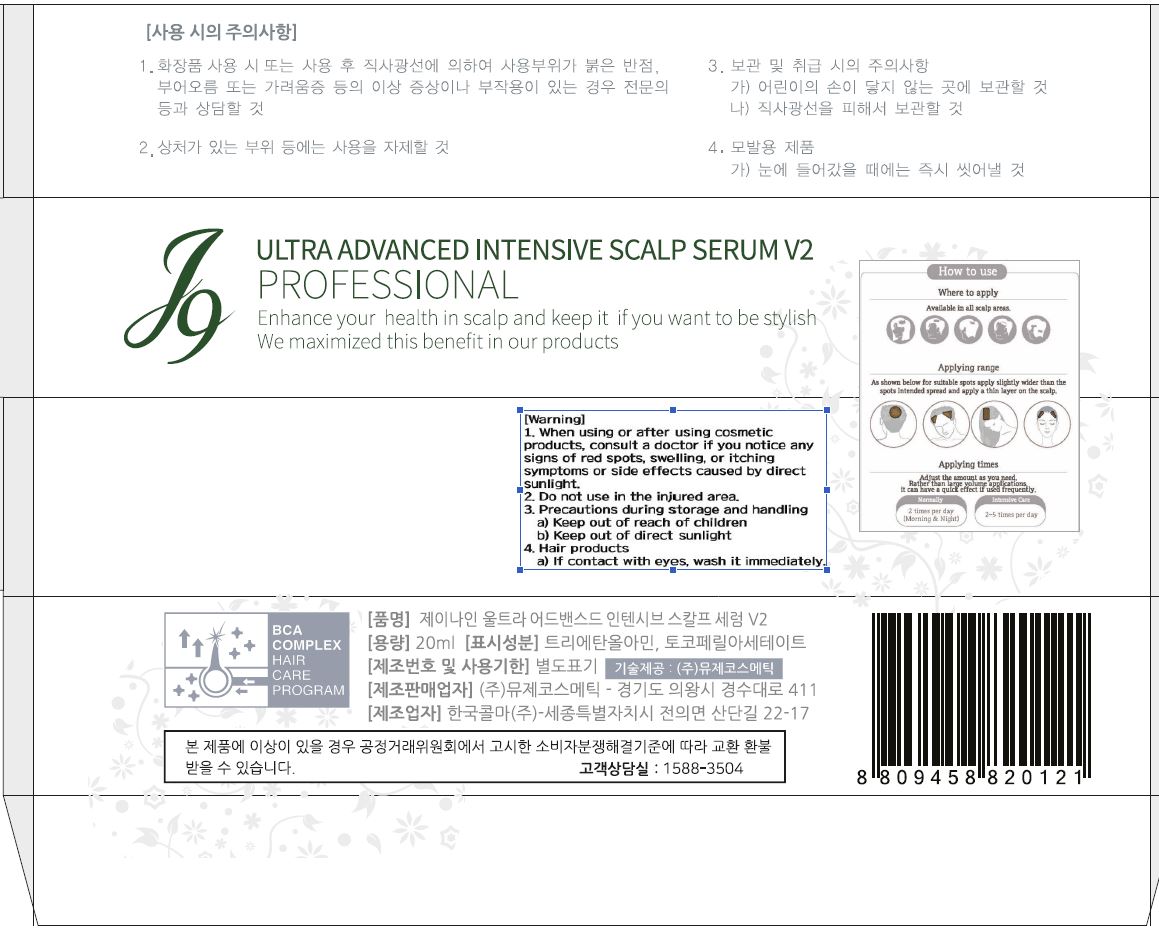 DRUG LABEL: J9 ULTRA ADVANCED INTENSIVE SCALP SERUM V2
NDC: 70488-0012 | Form: LIQUID
Manufacturer: MUSEE Cosmetic Co.,Ltd.
Category: otc | Type: HUMAN OTC DRUG LABEL
Date: 20190413

ACTIVE INGREDIENTS: NIACINAMIDE 0.001 g/100 mL
INACTIVE INGREDIENTS: WATER; BENTONITE

Drug Facts

ACTIVE INGREDIENT

niacinamide

INACTIVE INGREDIENT

WATER
ALCOHOL
BENTONITE
1,2-HEXANEDIOL
SORBITOL
WATER
CARBOMER
TRIETHANOLAMINE
FRAGRANCE
PEG-60 HYDROGENATED CASTOR OIL
ACRYLATES/C10-30 ALKYL ACRYLATE CROSSPOLYMER
DISODIUM EDTA
PERSEA GRATISSIMA (AVOCADO) OIL
TOCOPHERYL ACETATE
WATER
BUTYLENE GLYCOL
CHITOSAN SUCCINAMIDE

PURPOSE

enhance you health in scalp and akeep it if you want to be stylish

keep out of reach of the children

INDICATIONS AND USAGE

Apply to the scalp and gently rub it to absorb it

WARNINGS

1. when using or after using comsetic products, consult a doctor if you notice any signs of red spots, swelling, or itching symptoms or side effects caused by direct sunlight

2. do not use in the injured area

3. precautions during storage and handling

a) keep out of reach of children

b) keep out of direct sunlight

4. if contact with eyes, wash it immediately

DOSAGE AND ADMINISTRATION

for topical use only